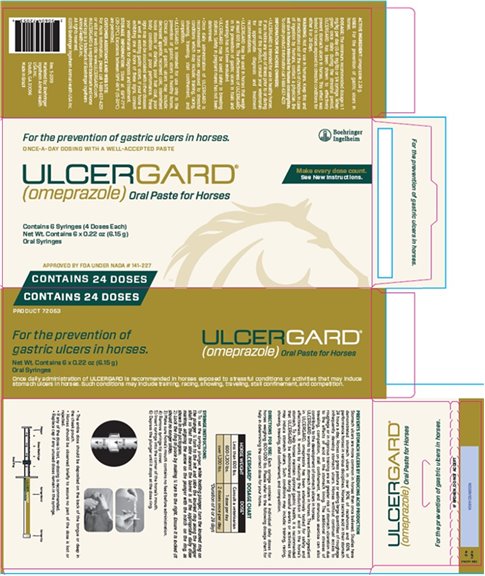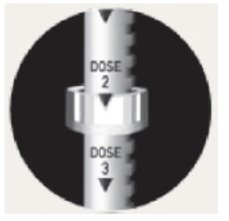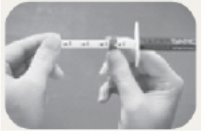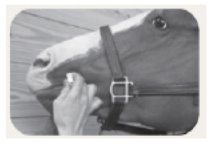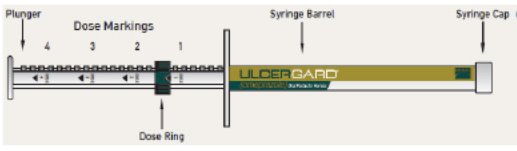 DRUG LABEL: ULCERGARD
NDC: 0010-9719 | Form: PASTE
Manufacturer: Boehringer Ingelheim Animal Health USA Inc.
Category: animal | Type: OTC ANIMAL DRUG LABEL
Date: 20201009

ACTIVE INGREDIENTS: omeprazole 370 mg/1 g

Ulcergard® (omeprazole) Oral Paste for Horses

PREVENTS STOMACH ULCERS BY REDUCING ACID PRODUCTION

Stomach ulcers are more common in horses than once believed. Studies have demonstrated stomach ulcers in over 90% of racehorses and 60% of performance horses in various disciplines. Horses secrete acid in their stomach 24 hours a day. Horses on grass pasture or eating large quantities of roughage infrequently develop stomach ulcers. Horses without continual access to roughage or in rigorous training are at greater risk of stomach ulceration due to the effects of acid on the stomach lining. The additional stresses of traveling, competition, stall confinement, and strenuous exercise can also contribute to the development of stomach ulcers in horses.

ULCERGARD works to prevent stomach ulcers in horses. The active ingredient in ULCERGARD, omeprazole has been extensively tested for safety and effectiveness. It works by reducing the production of acid in the horse's stomach. To help horses maintain optimal gastric health, it is recommended that ULCERGARD be administered during stressful events or activities that may induce stomach ulcers. Such conditions may include: training, racing, showing, traveling, stall confinement, and competition.

DIRECTIONS FOR USE

Each syringe contains 4 individual daily doses for horses weighing 600-1200 lbs. Please refer to the following dosage chart for help in determining the correct dose for your horse.

ULCERGARD® DOSAGE CHART

HORSE WEIGHT | DOSE*
Less than 600 lbs. | Consult a veterinarian
600-1,200 lbs. | 1 dose per day
over 1,200 lbs. | 2 doses once per day

*Duration of 8 or 28 days

SYRINGE INSTRUCTIONS:

1. To set the syringe plunger, while holding plunger, turn the knurled ring on the plunger ¼ turn to the left and slide the knurled ring along the plunger shaft so that the side nearest the barrel is at the appropriate daily dose marking, aligning the arrow on the plunger with the notch on the ring, as shown in the pictogram.
2. Lock the ring in place by making ¼ turn to the right. Ensure it is locked (it should no longer slide).
3. Make sure horse's mouth contains no feed before administration.
4. Remove syringe tip cover.
5. Insert syringe into the corner of the horse's mouth.
6. Depress the plunger until it stops at the dose ring.

- The entire dose should be deposited on the back of the tongue or deep in the cheek pouch.
- Horses should be observed briefly to assure no part of the dose is lost or rejected.
- If any of the dose is lost, re-dosing is recommended.
- Replace cap if any unused doses remain in the syringe.

ACTIVE INGREDIENT

Omeprazole 2.28 g.

USES

For the prevention of gastric ulcers in horses.

DOSAGE

The minimum recommended dosage is 1 mg/kg per day (0.45 mg/lb) or 1/4 syringe. When given once daily during the stressful period, ULCERGARD has been shown to effectively prevent stomach ulcers in horses. This effect was tested in horses exposed to stressful conditions for either 8 or 28 days.

WARNING

Not for use in humans. Keep this and all medications out of the reach of children. In case of ingestion by humans, contact a physician. Do not use in horses intended for human consumption. To obtain product information call 1-888-637-4251.

INFORMATION FOR HORSE OWNERS

- ULCERGARD is intended for use in healthy horses. If you notice any signs of illness prior to or during the use of this product, consult your veterinarian for appropriate diagnosis and treatment recommendations.
- ULCERGARD may be used in horses that weigh at least 600 lbs. The effectiveness of ULCERGARD in the prevention of gastric ulcers in foals and weanlings has not been evaluated.
- ULCERGARD may be used safely in breeding stallions. Safety in pregnant mares has not been determined.
- Once daily administration of ULCERGARD is recommended in horses exposed to stressful conditions which may include: training, racing, showing, traveling, stall confinement, and competition.
- ULCERGARD is intended for use only in the prevention of gastric ulcers in healthy horses. Clinical signs of gastric ulcers may include: decreased appetite, recurrent colic, intermittent loose stools or diarrhea, poor hair coat, poor body condition or poor performance. These signs may also be associated with other diseases as well as existing gastric ulcers. If your horse is exhibiting one or more of these signs, consult your veterinarian for diagnosis and treatment.

STORAGE INFORMATION

Store at 68°F-77°F (20-25°C). Excursions between 59°F-86°F (15-30°C) are permitted.

CUSTOMER ASSISTANCE AND WEB SITE

For more information, please call 1-888-637-4251 or visit our web site: www.ULCERGARD.com.

®ULCERGARD is a registered trademark and Horse Head logo is a trademark of Boehringer Ingelheim Animal Health USA Inc.

All rights reserved.

©2019 Boehringer Ingelheim Animal Health USA Inc.

603003511

Rev. 5-2019

Marketed by: Boehringer Ingelheim Animal Health USA Inc.
Duluth, GA 30096

Made in Brazil

Principal Display Panel – 6 syringe carton

For the prevention of gastric ulcers in horses.
ONCE-A-DAY DOSING WITH A WELL-ACCEPTED PASTE

ULCERGARD®
(omeprazole) Oral Paste for Horses

Contains 6 Syringes (4 Doses Each)
Net Wt. Contains 6 x 0.22 oz (6.15 g)
Oral Syringes

Approved by FDA under NADA # 141-227

CONTAINS 24 DOSES

Make every dose count.

See New Instructions.